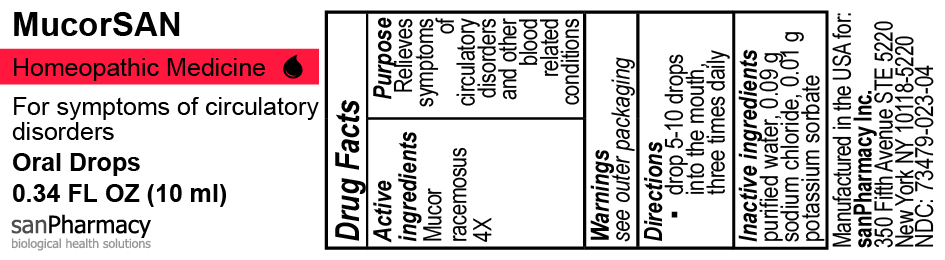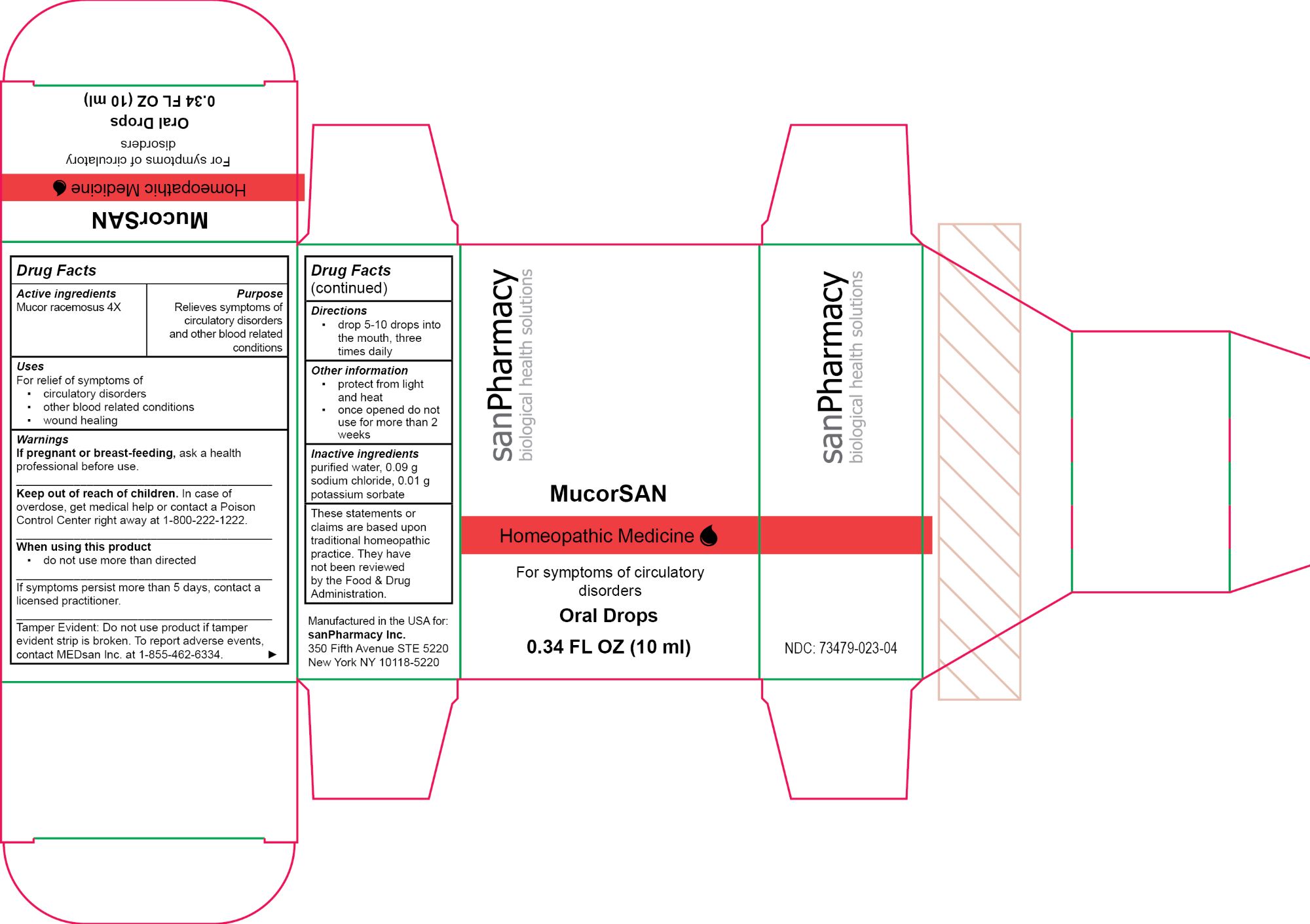 DRUG LABEL: MucorSAN
NDC: 73479-023 | Form: SOLUTION/ DROPS
Manufacturer: sanPharmacy Inc.
Category: homeopathic | Type: HUMAN OTC DRUG LABEL
Date: 20240425

ACTIVE INGREDIENTS: MUCOR RACEMOSUS 4 [hp_X]/10 mL
INACTIVE INGREDIENTS: WATER 10 mL/10 mL; SODIUM CHLORIDE 0.09 g/10 mL; POTASSIUM SORBATE 0.01 g/10 mL

MucorSAN Oral Drops

Indications

For symptoms of circulatory disorders

PURPOSE

Relieves symptoms of circulatory disorders and other blood related conditions

Dosage

drop 5-10 drops into the mouth, three times daily

Warinings

If pregnant or breast-feeding, ask a health professional before use.
______________________________
Keep out of reach of children. In case of overdose, get medical help or contact a Poison Control Center right away at 1-800-222-1222.
______________________________
When using this product
▪ do not use more than directed
______________________________
If symptoms persist more than 5 days, contact a licensed practitioner.
______________________________
Tamper Evident: Do not use product if tamper evident strip is broken. To report adverse events, contact MEDsan Inc. at 1-855-462-6334.

Keep out of reach of children. In case of overdose, get medical help or contact a Poison Control Center right away at 1-800-222-1222

Ingredients

Mucor racemosus 4X

INACTIVE INGREDIENT

purified water, 0.09 g sodium chloride, 0.01 g potassium sorbate

Warnings

If pregnant or breast-feeding, ask a health professional before use.
______________________________
Keep out of reach of children. In case of overdose, get medical help or contact a Poison Control Center right away at 1-800-222-1222.
______________________________
When using this product
▪ do not use more than directed
______________________________
If symptoms persist more than 5 days, contact a licensed practitioner.
______________________________
Tamper Evident: Do not use product if tamper evident strip is broken. To report adverse events, contact MEDsan Inc. at 1-855-462-6334.

Keep out of reach of children. In case of overdose, get medical help or contact a Poison Control Center right away at 1-800-222-1222

Manufactured in the USA for:
sanPharmacy Inc.
350 Fifth Avenue STE 5220
New York NY 10118-5220

Liability statement

These statements or claims are based upon traditional homeopathic practice. They have not been reviewed by the Food & Drug Administration

STORAGE AND HANDLING

protect from light and heat

once opened do not use for more than 2 weeks

Principal Display Panel

MucorSAN

Homeopathic Medicine

For symptoms of circulatory disorders

Oral Drops

0.34 FL OZ (10 ml)

sanPharmacy

biological health solutions